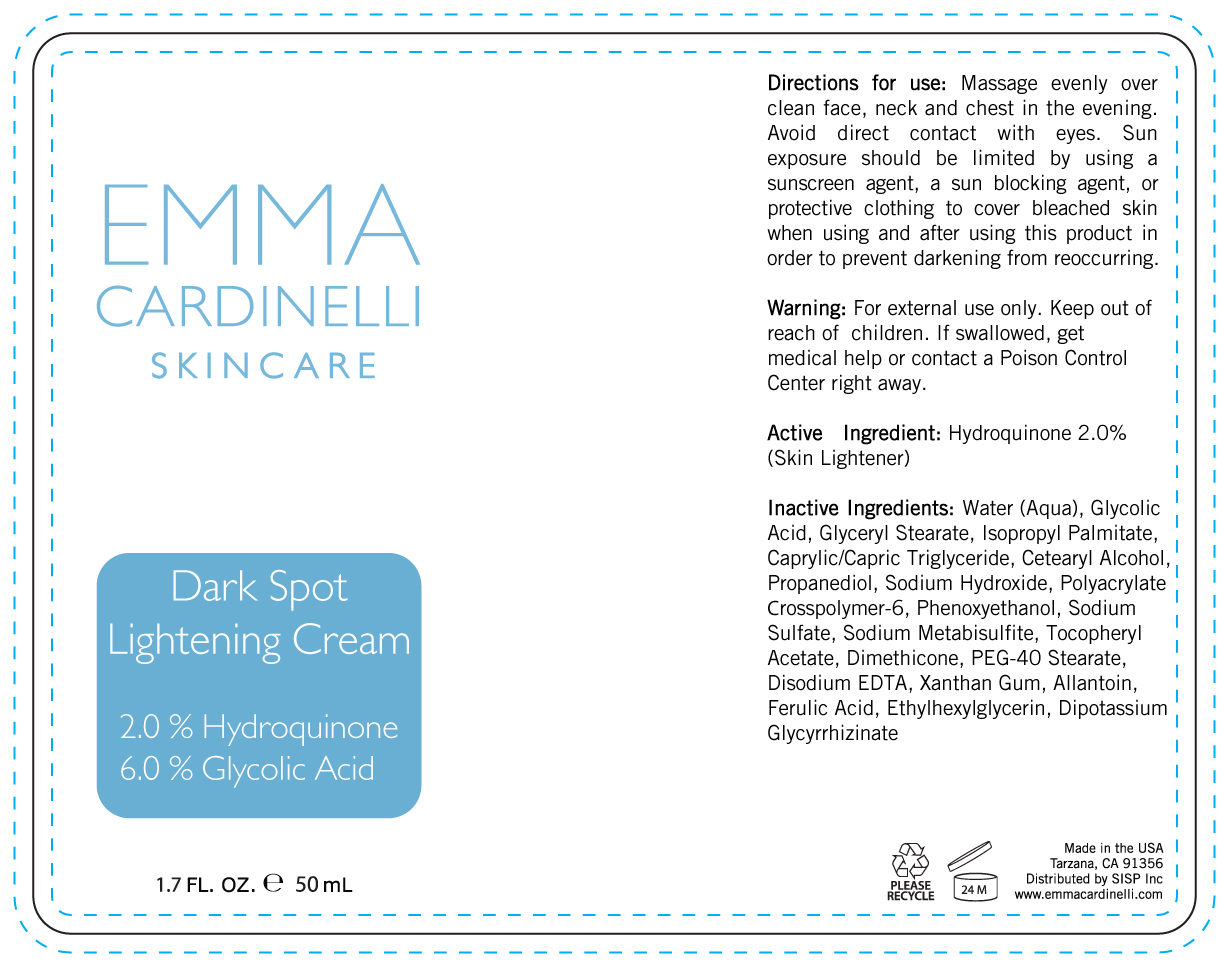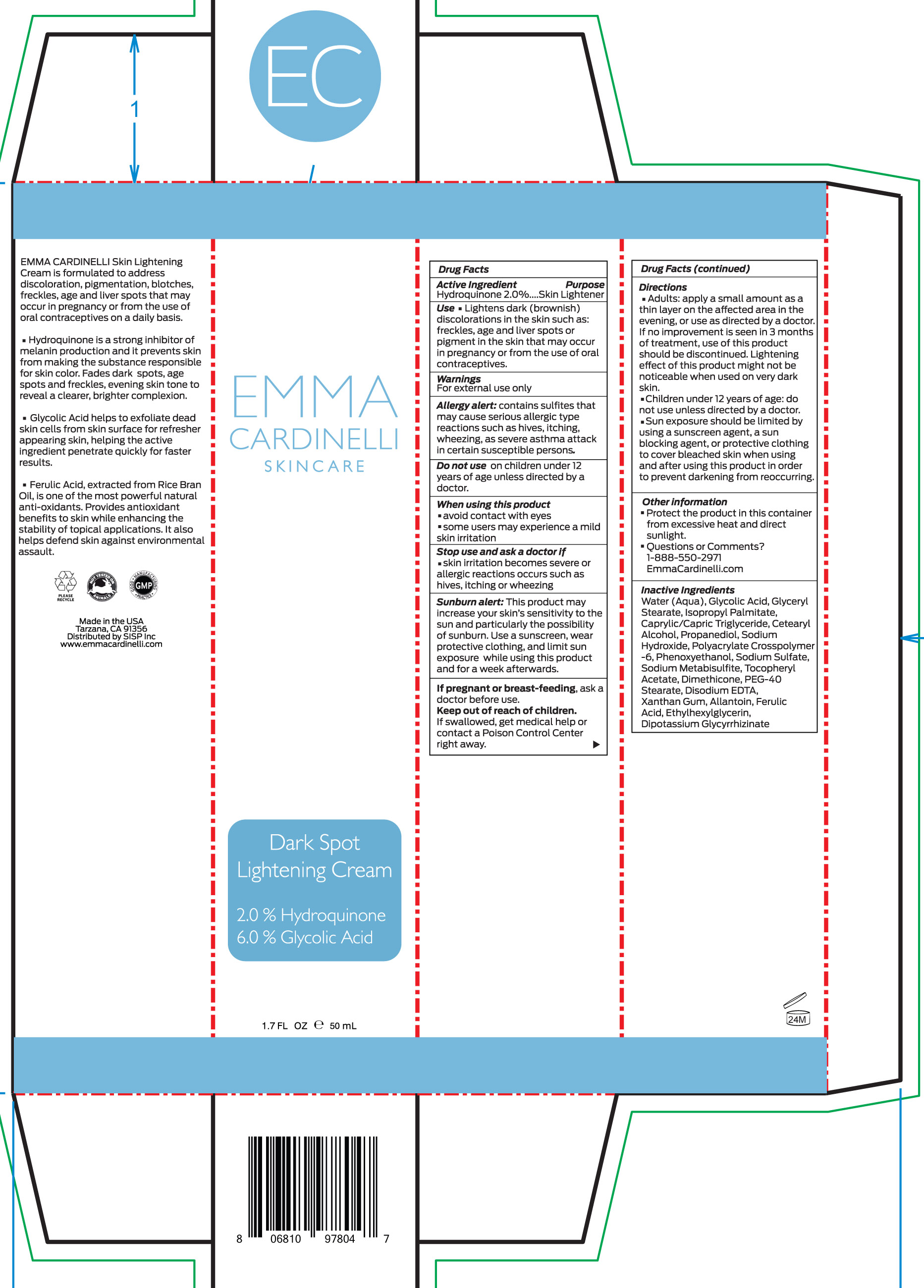 DRUG LABEL: Dark Spot Lightening Cream
NDC: 56152-4002 | Form: CREAM
Manufacturer: Cosmetic Enterprises Ltd.
Category: otc | Type: HUMAN OTC DRUG LABEL
Date: 20181221

ACTIVE INGREDIENTS: HYDROQUINONE 2 g/100 mL
INACTIVE INGREDIENTS: CETOSTEARYL ALCOHOL; PROPANEDIOL; AMMONIUM ACRYLOYLDIMETHYLTAURATE, DIMETHYLACRYLAMIDE, LAURYL METHACRYLATE AND LAURETH-4 METHACRYLATE COPOLYMER, TRIMETHYLOLPROPANE TRIACRYLATE CROSSLINKED (45000 MPA.S); SODIUM SULFATE; SODIUM METABISULFITE; DIMETHICONE; PEG-40 STEARATE; FERULIC ACID; ALLANTOIN, (+)-; ETHYLHEXYLGLYCERIN; SODIUM HYDROXIDE; PHENOXYETHANOL; .ALPHA.-TOCOPHEROL ACETATE, D-; ISOPROPYL PALMITATE; GLYCERYL MONOSTEARATE; MEDIUM-CHAIN TRIGLYCERIDES; WATER; GLYCOLIC ACID; EDETATE DISODIUM; XANTHAN GUM; GLYCYRRHIZINATE DIPOTASSIUM

Dark Spot Lightening Cream

Active ingredient Purpose

Hydroquinone 2% Skin lightener

Use

Lightens dark (brownish) discolorations in the skin such as: freckles, age and liver spots or pigment in the skin that may occur in pregnancy or from the use of oral contraceptives

Keep out of reach of children . If swallowed, get medical help or contact a Poison Control Center right away.

Stop use and ask a doctor if

- Skin irritation becomes severe or allergic reaction occurs such as hives, itching, or wheezing

Warnings

For external use only

Allergy alert: contains sulfites that may cause serious allergic type reactions such as hives, itching, wheezing as severe asthma attack in certain susceptible persons.

Do not use on children under 12 years of age unless directed by a doctor

When using this product

- avoid contact with eyes
- some users may experience a mild skin irritatiion\

Sunburn alert: This product may increase your skin's sensitivity to the sun and particularly the possibility of sunburn. Use a sunscreen, wear protective clothing and limit sun exposure while using this product and for a week afterwards.

If pregnant or breast-feeding, ask a doctor before use.

Directions

- Adults: apply a small amount as a thin layer on the affected area in the evening, or use as directed by a doctor. If no improvement is seen in 3 months of treatment, use of this product should be discontinued. Lightening effect of this product might not be noticeable when used on very dark skin.
- Children under 12 years of age: do not use unless directed by a doctor.
- Sun Exposure should be limited by using a sunscreen agent, a sun blocking agent, or protective clothing to cover bleached skin when using and after using this product in order to prevent darkening from reoccurring.

INACTIVE INGREDIENT

Water (Aqua), Glycolic Acid, Glyceryl Stearate, Isopropyl Palmitate, Caprylic/Capric Triglyceride, Cetearyl Alcohol, Propanediol, Sodium Hydroxide, Polyacrylate Crosspolymer-6, Phenoxyethanol, Sodium Sulfate, Sodium Metabisulfite, Tocopheryl Acetate, Dimethicone, PEG-40 Stearate, Disodium EDTA, Xantan Gum, Allantoin, Ferulic Acid, Ethylhexylglycerin, Dipotassium Glycyrrhizate

PACKAGE LABEL

Dark Spot Lightening Cream

2% Hydroquinone

6% Glycolic Acid

1.7 FL OZ 50mL